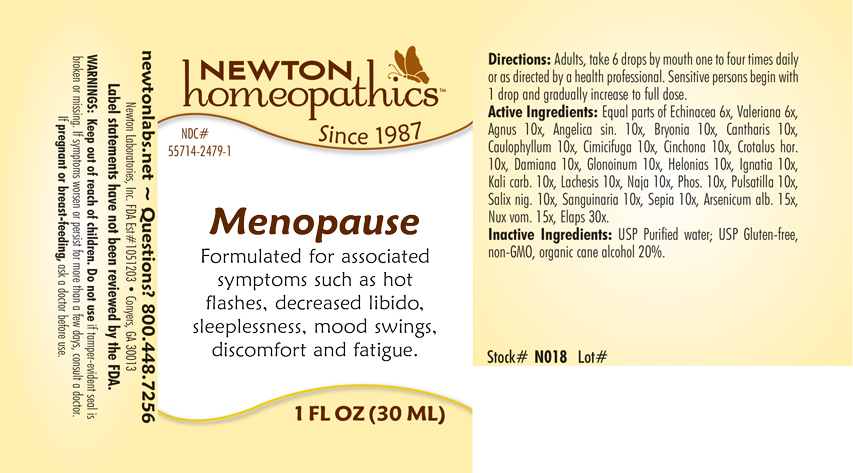 DRUG LABEL: Menopause
NDC: 55714-2479 | Form: LIQUID
Manufacturer: Newton Laboratories, Inc.
Category: homeopathic | Type: HUMAN OTC DRUG LABEL
Date: 20250207

ACTIVE INGREDIENTS: MICRURUS CORALLINUS VENOM 30 [hp_X]/1 mL; CHASTE TREE FRUIT 10 [hp_X]/1 mL; ANGELICA SINENSIS ROOT 10 [hp_X]/1 mL; ARSENIC TRIOXIDE 15 [hp_X]/1 mL; BRYONIA ALBA ROOT 10 [hp_X]/1 mL; LYTTA VESICATORIA 10 [hp_X]/1 mL; CAULOPHYLLUM THALICTROIDES ROOT 10 [hp_X]/1 mL; BLACK COHOSH 10 [hp_X]/1 mL; CINCHONA OFFICINALIS BARK 10 [hp_X]/1 mL; CROTALUS HORRIDUS HORRIDUS VENOM 10 [hp_X]/1 mL; TURNERA DIFFUSA LEAFY TWIG 10 [hp_X]/1 mL; NITROGLYCERIN 10 [hp_X]/1 mL; CHAMAELIRIUM LUTEUM ROOT 10 [hp_X]/1 mL; STRYCHNOS IGNATII SEED 10 [hp_X]/1 mL; POTASSIUM CARBONATE 10 [hp_X]/1 mL; LACHESIS MUTA VENOM 10 [hp_X]/1 mL; NAJA NAJA VENOM 10 [hp_X]/1 mL; STRYCHNOS NUX-VOMICA SEED 15 [hp_X]/1 mL; PHOSPHORUS 10 [hp_X]/1 mL; ANEMONE PULSATILLA 10 [hp_X]/1 mL; SALIX NIGRA BARK 10 [hp_X]/1 mL; SANGUINARIA CANADENSIS ROOT 10 [hp_X]/1 mL; SEPIA OFFICINALIS JUICE 10 [hp_X]/1 mL; ECHINACEA, UNSPECIFIED 6 [hp_X]/1 mL; VALERIAN 6 [hp_X]/1 mL
INACTIVE INGREDIENTS: ALCOHOL; WATER

Menopause 2479L

INDICATIONS & USAGE SECTION

Formulated for associated symptoms such as hot flashes, decreased libido, sleeplessness, mood swings, discomfort and fatigue.

DOSAGE & ADMINISTRATION SECTION

Directions: Adults, take 6 drops by mouth one to four times daily or as directed by a health professional. Sensitive persons begin with 1 drop and gradually increase to full dose.

OTC - ACTIVE INGREDIENT SECTION

Equal parts of Echinacea 6x, Valeriana officinalis 6x, Agnus castus 10x, Angelica sinensis radix 10x, Bryonia 10x, Cantharis 10x, Caulophyllum thalictroides 10x, Cimicifuga racemosa 10x, Cinchona officinalis 10x, Crotalus horridus 10x, Damiana 10x, Glonoinum 10x, Helonias dioica 10x, Ignatia amara 10x, Kali carbonicum 10x, Lachesis mutus 10x, Naja tripudians 10x, Phosphorus 10x, Pulsatilla 10x, Salix nigra 10x, Sanguinaria canadensis 10x, Sepia 10x, Arsenicum album 15x, Nux vomica 15x, Elaps corallinus 30x.

OTC - PURPOSE SECTION

Formulated for associated symptoms such as hot flashes, decreased libido, sleeplessness, mood swings, discomfort and fatigue.

INACTIVE INGREDIENT SECTION

Inactive Ingredients: USP Purified Water; USP Gluten-free, non-GMO, organic cane alcohol 20%.

QUESTIONS SECTION

newtonlabs.net – Questions? 800.448.7256

Newton Laboratories, Inc. FDA Est # 1051203 - Conyers, GA 30013

WARNINGS SECTION

WARNINGS: Keep out of reach of children. Do not use if tamper-evident seal is broken or missing. If symptoms worsen or persist for more than a few days, consult a doctor. If pregnant or breast-feeding, ask a doctor before use.

OTC - PREGNANCY OR BREAST FEEDING SECTION

If pregnant or breast-feeding, ask a doctor before use.

OTC - KEEP OUT OF REACH OF CHILDREN SECTION

Keep out of reach of children